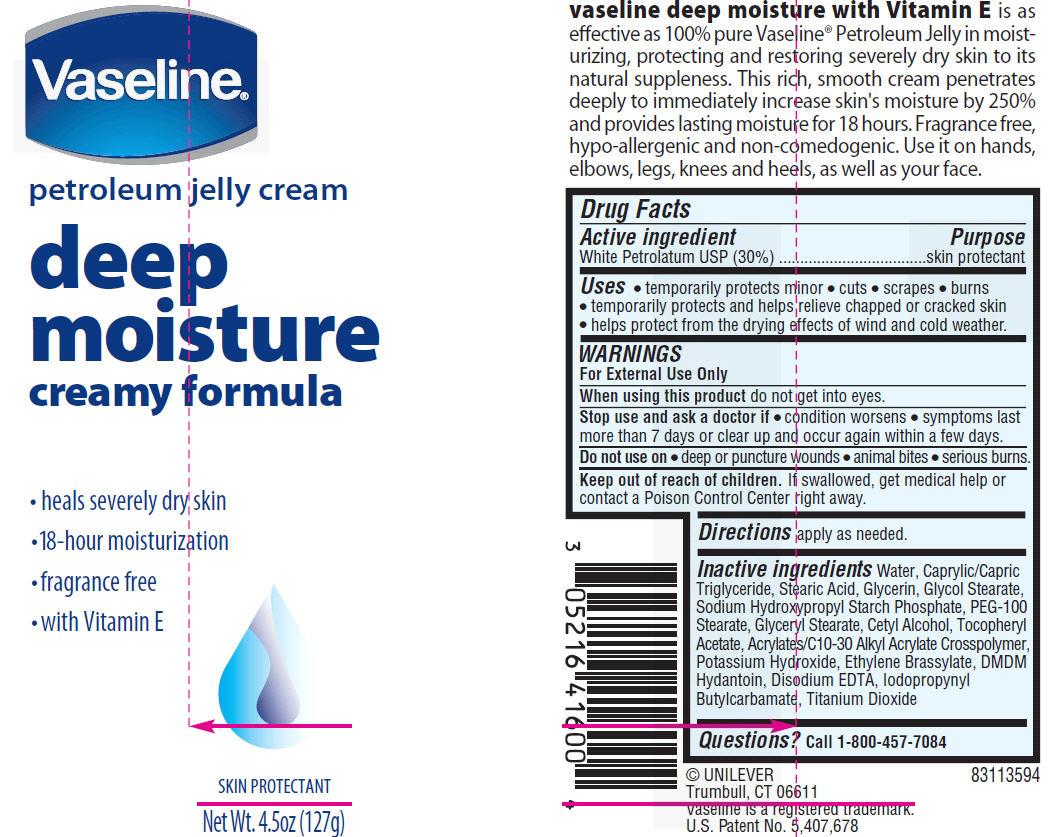 DRUG LABEL: Vaseline
NDC: 64942-0276 | Form: CREAM
Manufacturer: Conopco Inc. d/b/a Unilever
Category: otc | Type: HUMAN OTC DRUG LABEL
Date: 20120530

ACTIVE INGREDIENTS: petrolatum 30 g/100 g
INACTIVE INGREDIENTS: WATER; MEDIUM-CHAIN TRIGLYCERIDES; STEARIC ACID; GLYCERIN; GLYCOL STEARATE; PEG-100 STEARATE; GLYCERYL MONOSTEARATE; CETYL ALCOHOL; .ALPHA.-TOCOPHEROL ACETATE, D-; POTASSIUM HYDROXIDE; ETHYLENE BRASSYLATE; DMDM HYDANTOIN; EDETATE DISODIUM; IODOPROPYNYL BUTYLCARBAMATE; TITANIUM DIOXIDE

Vaseline Petroleum Jelly Cream Deep Moisture PDP and drug facts

Active ingredient
WHITE PETROLATUM USP (30%)

Purpose
skin protectant

Uses
●temporarily protects minor ● cuts ● scrapes ● burns
● temporarily protects and helps relieve chapped or cracked skin
● helps protect from the drying effects of wind and cold weather

WARNINGS
For External Use Only

When using this product do not get into eyes.

Stop use and ask a doctor if ● condition worsens ● symptoms last more than 7 days or clear up and occur again within a few days.

Do not use on ● deep or puncture wounds ● animal bites ● serious burns

Keep out of reach of children. If swallowed get medical help or contact a Poison Control Center right away.

DOSAGE AND ADMINISTRATION

Directions apply as needed.

Inactive ingredients Water, Caprylic/Capric Triglyceride, Stearic
Acid, Glycerin, Glycol Stearate, Sodium Hydroxypropyl Starch
Phosphate, PEG-100 Stearate, Glyceryl Stearate, Cetyl Alcohol,
Tocopheryl Acetate, Acrylates/C10-30 Alkyl Acrylate Crosspolymer,
Potassium Hydroxide, Ethylene Brassylate, DMDM Hydantoin,
Disodium EDTA, Iodopropynyl Butylcarbamate, Titanium Dioxide

Questions? Call 1-800-457-7084

PACKAGE LABEL

VPJ Cream Deep Moisture PDP